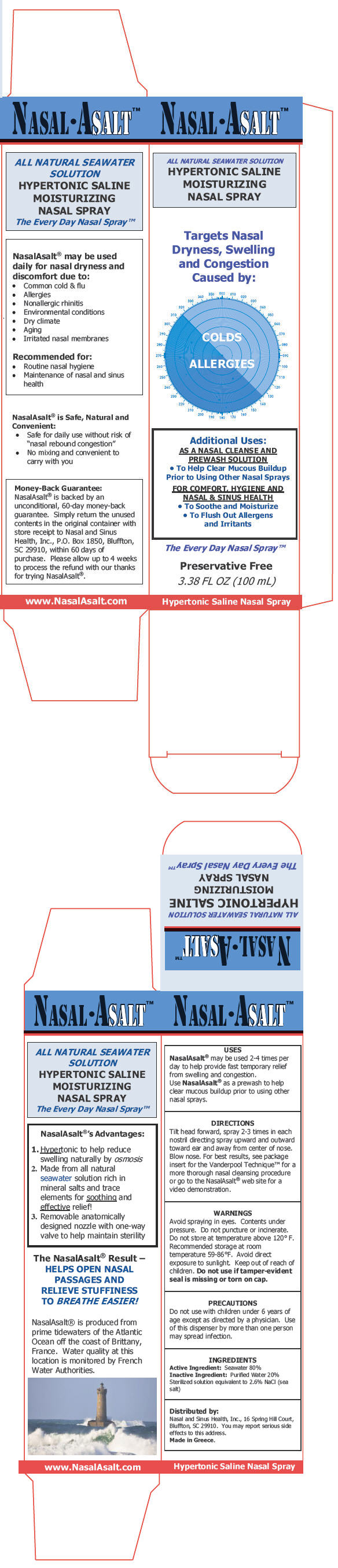 DRUG LABEL: NasalAsalt 
NDC: 52429-123 | Form: SPRAY
Manufacturer: Nasal and Sinus Health, Inc.
Category: otc | Type: HUMAN OTC DRUG LABEL
Date: 20110926

ACTIVE INGREDIENTS: Sodium Chloride 2600 mg/100 mL
INACTIVE INGREDIENTS: water

NASAL•ASALT™
ALL NATURAL SEAWATER SOLUTION
HYPERTONIC SALINE
MOISTURIZING
NASAL SPRAY

USES

PURPOSE

NasalAsalt® may be used 2-4 times per day to help provide fast temporary relief from swelling and congestion.

Use NasalAsalt® as a prewash to help clear mucous buildup prior to using other nasal sprays.

DIRECTIONS

Tilt head forward, spray 2-3 times in each nostril directing spray upward and outward toward ear and away from center of nose. Blow nose. For best results, see package insert for the Vanderpool Technique™ for a more thorough nasal cleansing procedure or go to the NasalAsalt® web site for a video demonstration.

WARNINGS

WHEN USING

Avoid spraying in eyes. Contents under pressure. Do not puncture or incinerate. Do not store at temperature above 120° F. Recommended storage at room temperature 59-86°F. Avoid direct exposure to sunlight.

Keep out of reach of children.

Do not use if tamper-evident seal is missing or torn on cap.

PRECAUTIONS

Do not use with children under 6 years of age except as directed by a physician. Use of this dispenser by more than one person may spread infection.

ACTIVE INGREDIENT

INACTIVE INGREDIENT

INGREDIENTS

Active Ingredient: Seawater 80%

Inactive Ingredient: Purified Water 20% Sterilized solution equivalent to 2.6% NaCl (sea salt)

Distributed by:

Nasal and Sinus Health, Inc., 16 Spring Hill Court, Bluffton, SC 29910. You may report serious side effects to this address.

PRINCIPAL DISPLAY PANEL - 100 mL Canister Carton

NASAL•ASALT™

ALL NATURAL SEAWATER SOLUTION
HYPERTONIC SALINE
MOISTURIZING
NASAL SPRAY

Targets Nasal
Dryness, Swelling
and Congestion
Caused by:

COLDS
ALLERGIES

Additional Uses:
AS A NASAL CLEANSE AND
PREWASH SOLUTION

- To Help Clear Mucous Buildup
  Prior to Using Other Nasal Sprays

FOR COMFORT, HYGIENE AND
NASAL & SINUS HEALTH

- To Soothe and Moisturize
- To Flush Out Allergens
  and Irritants

The Every Day Nasal Spray™

Preservative Free

3.38 FL OZ (100 mL)

Hypertonic Saline Nasal Spray